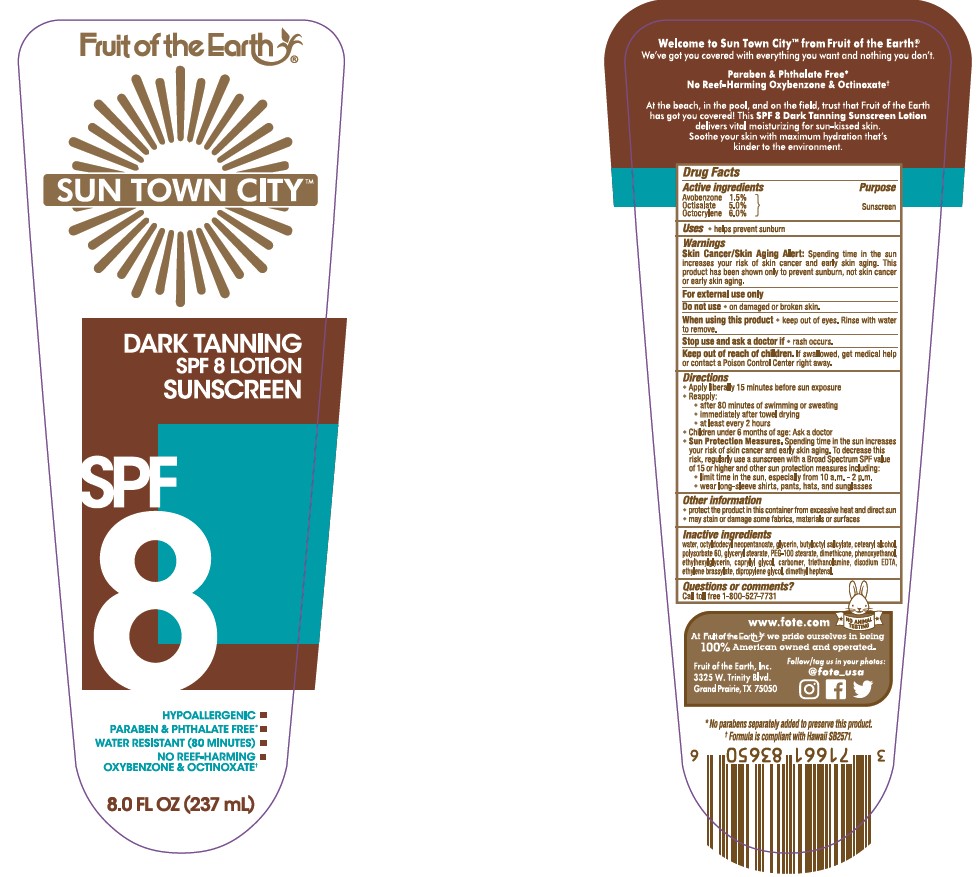 DRUG LABEL: Fruit of the Earth Sun Town City Dark Tanning SPF 8 Sunscreen
NDC: 62217-072 | Form: LOTION
Manufacturer: Fruit of the Earth, Inc.
Category: otc | Type: HUMAN OTC DRUG LABEL
Date: 20241017

ACTIVE INGREDIENTS: AVOBENZONE 15 mg/1 mL; OCTISALATE 50 mg/1 mL; OCTOCRYLENE 60 mg/1 mL
INACTIVE INGREDIENTS: WATER; GLYCERIN; OCTYLDODECYL NEOPENTANOATE; BUTYLOCTYL SALICYLATE; CETOSTEARYL ALCOHOL; POLYSORBATE 60; DIMETHICONE; PHENOXYETHANOL; CAPRYLYL GLYCOL; CARBOMER INTERPOLYMER TYPE A (55000 CPS); ETHYLHEXYLGLYCERIN; TROLAMINE; ETHYLENE BRASSYLATE; DIPROPYLENE GLYCOL; 2,6-DIMETHYL-5-HEPTENAL; GLYCERYL 1-STEARATE; PEG-100 STEARATE; EDETATE DISODIUM

Fruit of the Earth Sun Town City Dark Tanning SPF 8 Lotion Sunscreen

Active ingredients

Avobenzone 1.5%, Octisalate 5.0%, Octocrylene 6.0%

Purpose

Sunscreen

Uses

• helps prevent sunburn

Warnings

Skin Cancer/Skin Aging Alert: Spending time in the sun increases your risk of skin cancer and early skin aging. This product has been shown only to prevent sunburn, not skin cancer or early skin aging.

For external use only

Do not use

• on damaged or broken skin.

When using this product

• keep out of eyes. Rinse with water to remove.

Stop use and ask a doctor if

• rash occurs.

Keep out of reach of children.

If swallowed, get medical help or contact a Poison Control Center right away.

Directions

- Apply liberally 15 minutes before sun exposure
- Reapply:

• after 80 minutes of swimming or sweating

• immediately after towel drying

• at least every 2 hours

- Children under 6 months of age: Ask a doctor
- Sun Protection Measures. Spending time in the sun increases your risk of skin cancer and early skin aging. To decrease this risk, regularly use a sunscreen with a Broad Spectrum SPF value of 15 or higher and other sun protection measures including:

• limit time in the sun, especially from 10 a.m.-2 p.m.

•wear long-sleeved shirts, pants, hats, and sunglasses

Other information

- protect the product in this container from excessive heat and direct sun
- may stain or damage some fabrics, materials or surfaces

Inactive ingredients

water, octyldodecyl neopentanoate, glycerin, butyloctyl salicylate, cetearyl alcohol, polysorbate 60, glyceryl stearate, PEG-100 stearate, dimethicone, phenoxyethanol, ethylhexylglycerin, caprylyl glycol, carbomer, triethanolamine, disodium EDTA, ethylene brassylate, dipropylene glycol, dimethyl heptenal.